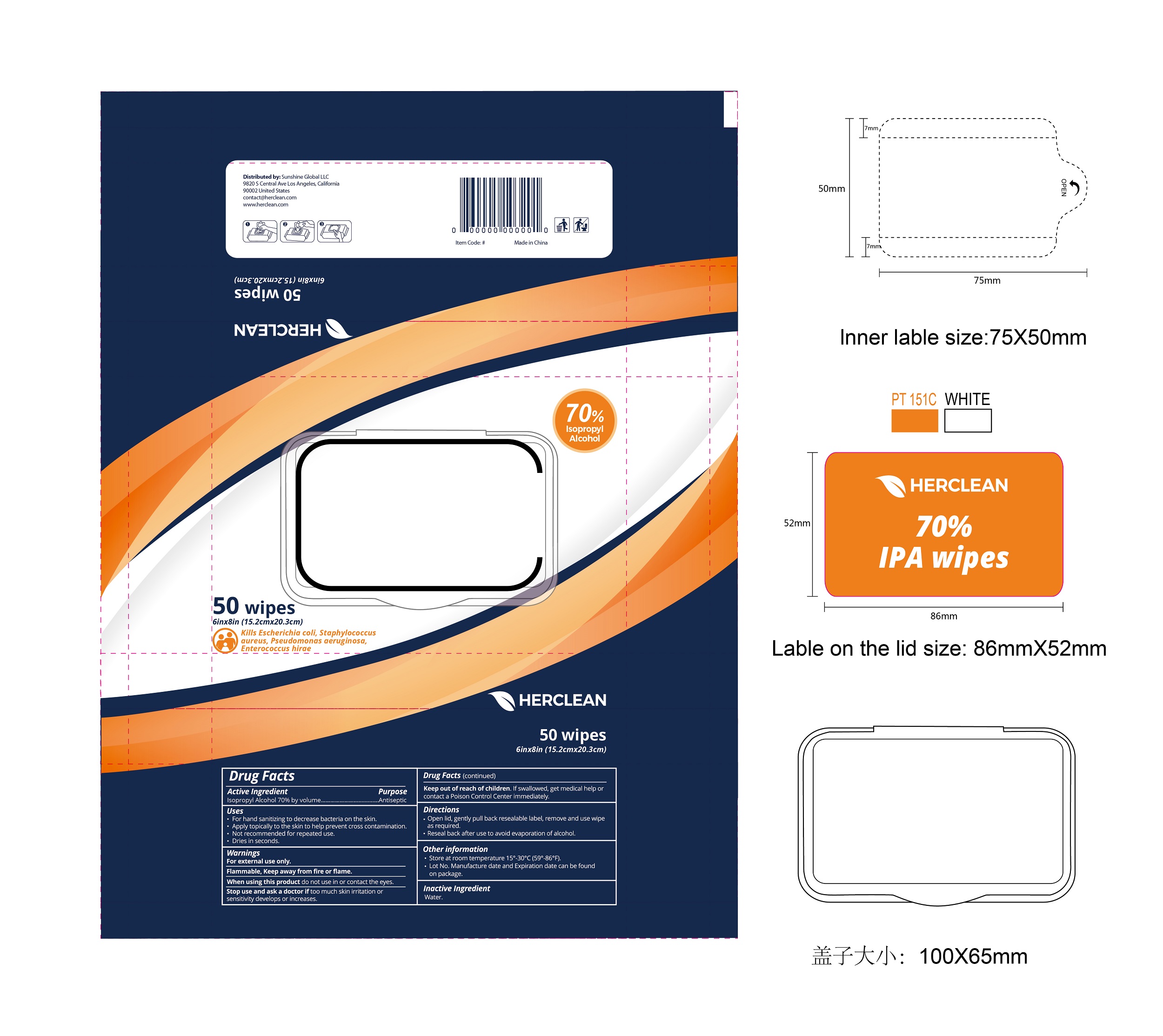 DRUG LABEL: Herclean IPA Wipes
NDC: 75109-516 | Form: CLOTH
Manufacturer: Kangna (Zhejiang) Medical Supplies Co., Ltd.
Category: otc | Type: HUMAN OTC DRUG LABEL
Date: 20220114

ACTIVE INGREDIENTS: ISOPROPYL ALCOHOL 70 mL/100 mL
INACTIVE INGREDIENTS: WATER

75109-516 Herclean IPA Wipes 70% Isopropyl Alcohol

Active Ingredient

Isopropyl Alcohol 70% by volume

Purpose

Antiseptic

USE

Uses■for hand sanitizing to decrease bacteria on the skin■apply
topically to the skin to help prevent cross contamination■not recommended
for repeated use■dries in seconds

Warning

For external use only. Flammable, keep away from fire or flame.
When using this product keep out of eyes, ears, and mouth. In case of eye contact, flush thoroughly with water.
Stop use and ask doctor if too much skin irritation or sensitivity develops or increases.

Keep out of reach of children. If swallowed, get medical help or contact a Posion Control Center immediately.

Directions

.Open lid, gently pull back resealable label, remove and use wipe as required.
Reseal back after use to avoid evaporation of alcohol.
Other information
.Store at room temperature 15°-30°C (59°-86°F).
. Lot No. Manufacture date and Expiration date can be found on package.

Inactive ingredients

Water